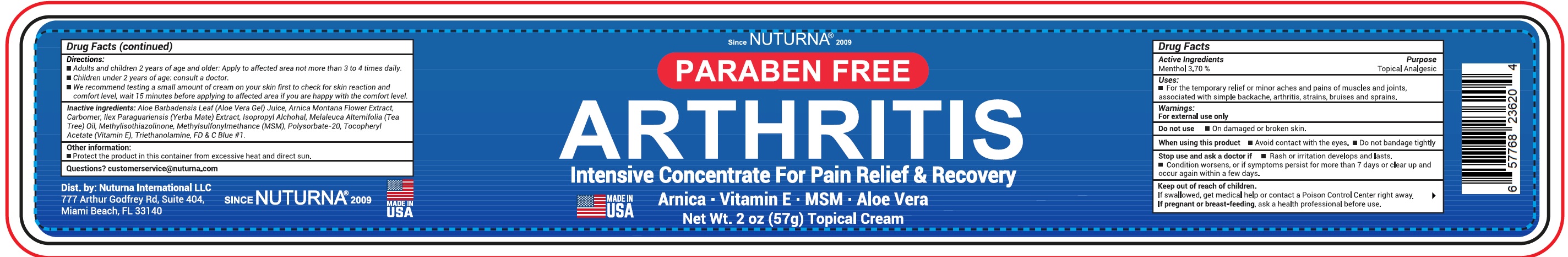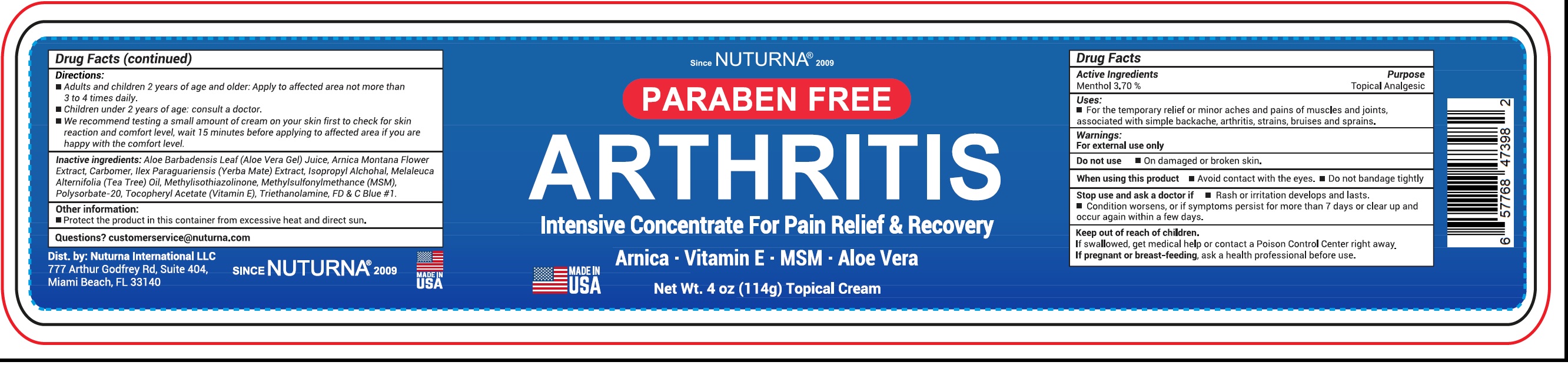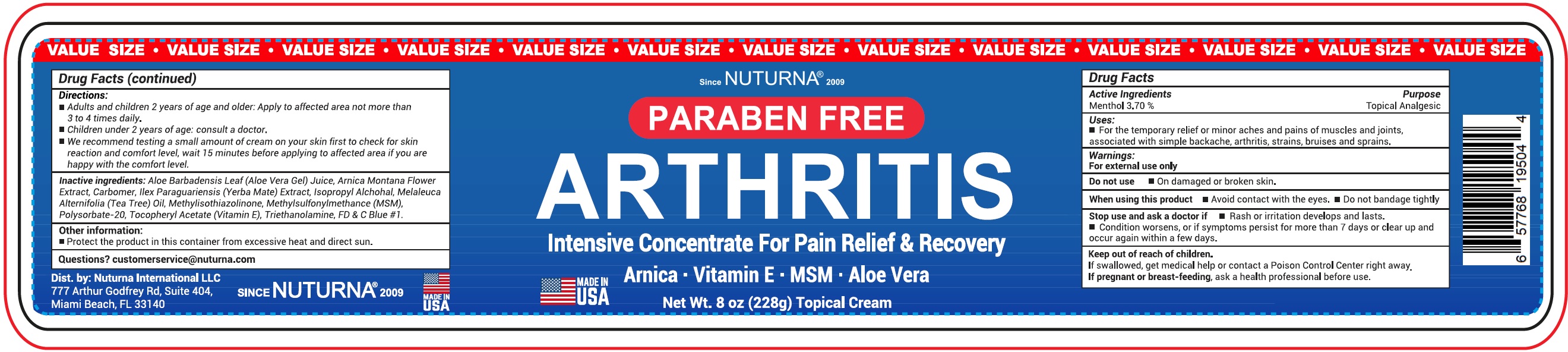 DRUG LABEL: NUTURNA Arthritis Intensive Concentrate for Pain Relief and  Recovery
NDC: 81996-244 | Form: CREAM
Manufacturer: Nuturna International LLC
Category: otc | Type: HUMAN OTC DRUG LABEL
Date: 20240104

ACTIVE INGREDIENTS: MENTHOL 3.7 g/100 g
INACTIVE INGREDIENTS: ALOE VERA LEAF; ARNICA MONTANA FLOWER; ILEX PARAGUARIENSIS LEAF; ISOPROPYL ALCOHOL; TEA TREE OIL; METHYLISOTHIAZOLINONE; DIMETHYL SULFONE; POLYSORBATE 20; .ALPHA.-TOCOPHEROL ACETATE; TROLAMINE; FD&C BLUE NO. 1

NUTURNA (as PLD) - Arthritis Intensive Concentrate for Pain Relief & Recovery (81996-244)

Active Ingredients

Menthol 3.70%

Purpose

Topical Analgesic

Uses:

- For the temporary relief of minor aches and pains of muscles and joints, associated with simple backache, arthritis, strains, bruises and sprains.

Warnings:

For external use only

Do not use

- On damaged or broken skin.

When using this product

- Avoid contact with the eyes.
- Do not bandage tightly

Stop use and ask a doctor if

- Rash or irritation develops and lasts.
- Condition worsens, or if symptoms persist for more than 7 days or clear up and occurs again within a few days.

Keep out of reach of children.

If swallowed, get medical help or contact a Poison Control Center right away.

If pregnant or breast-feeding,

ask a health professional before use.

Directions:

- Adults and children 2 years of age and older: Apply to affected area not more than 3 to 4 times daily.
- Children under 2 years of age: consult a doctor.
- We recommend testing a small amount of cream on your skin first to check for skin reaction and comfort level, wait 15 minutes before applying to affected area if you are happy with the comfort level.

Inactive ingredients:

Aloe Barbadensis Leaf(Aloe Vera Gel)Juice, Arnica Montana Flower Extract, Carbomer, Ilex Paraguariensis (Yerba Mate) Extract, Isopropyl Alcohol, Melaleuca Alternifolia (Tea Tree) Oil, Methylisothiazolinone, Methylsulfonylmethane (MSM), Polysorbate-20, Tocopheryl Acetate (Vitamin E), Triethanolamine, FD & C Blue # 1.

Other information:

- Protect the product in this container from excessive heat and direct sun.

Questions ?

customerservice@nuturna.com